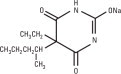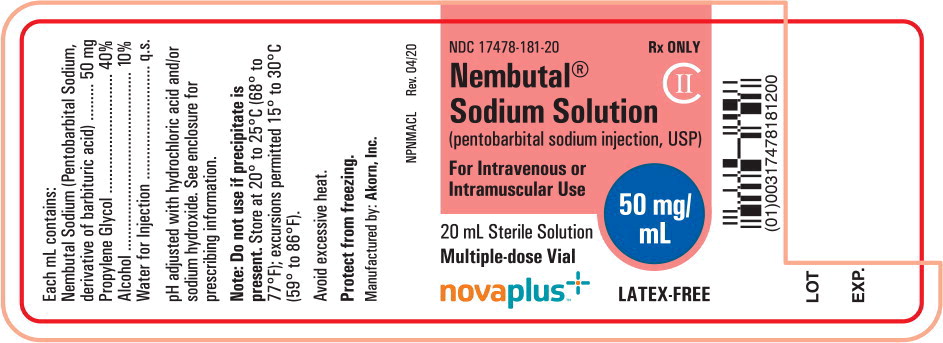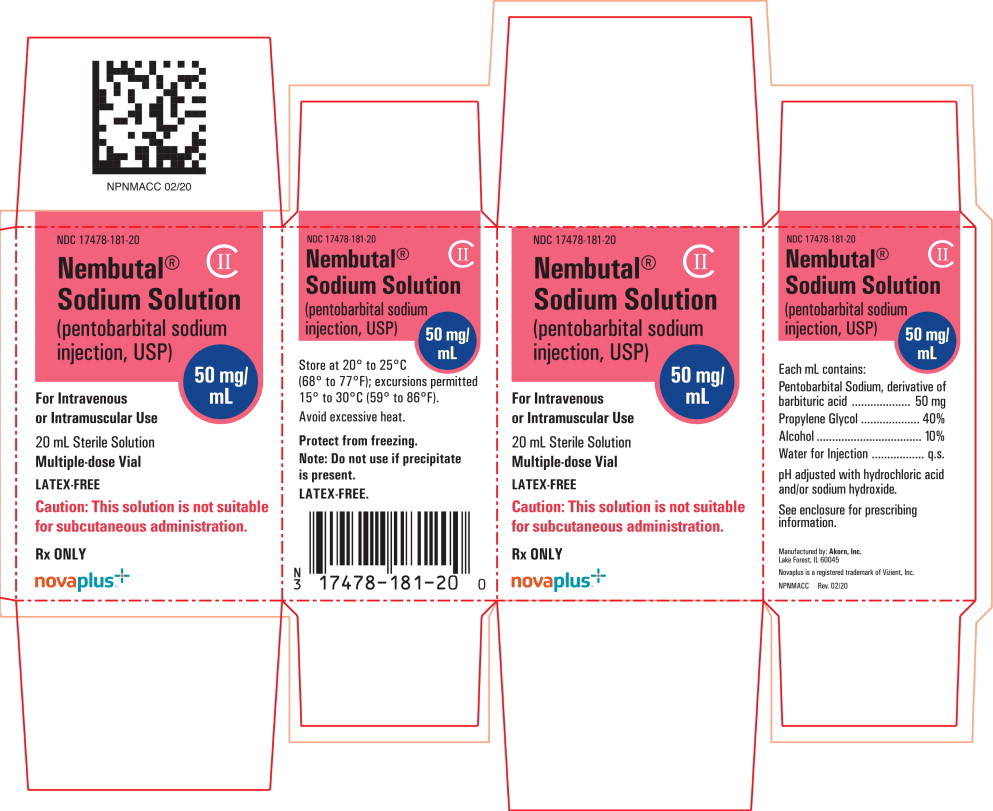 DRUG LABEL: Pentobarbital Sodium
NDC: 17478-181 | Form: INJECTION
Manufacturer: Akorn
Category: prescription | Type: HUMAN PRESCRIPTION DRUG LABEL
Date: 20240201
DEA Schedule: CII

ACTIVE INGREDIENTS: Pentobarbital Sodium 50 mg/1 mL
INACTIVE INGREDIENTS: Propylene Glycol; Alcohol; Water; Hydrochloric Acid; Sodium Hydroxide

Nembutal® Sodium Solution CII

(pentobarbital sodium injection, USP)

novaplus TM^+
Rx only

Vials

DO NOT USE IF MATERIAL HAS PRECIPITATED

DESCRIPTION

The barbiturates are nonselective central nervous system depressants which are primarily used as sedative hypnotics and also anticonvulsants in subhypnotic doses. The barbiturates and their sodium salts are subject to control under the Federal Controlled Substances Act (See “Drug Abuse and Dependence” section).

The sodium salts of amobarbital, pentobarbital, phenobarbital, and secobarbital are available as sterile parenteral solutions.

Barbiturates are substituted pyrimidine derivatives in which the basic structure common to these drugs is barbituric acid, a substance which has no central nervous system (CNS) activity. CNS activity is obtained by substituting alkyl, alkenyl, or aryl groups on the pyrimidine ring.

NEMBUTAL Sodium Solution (pentobarbital sodium injection) is a sterile solution for intravenous or intramuscular injection. Each mL contains pentobarbital sodium 50 mg, in a vehicle of propylene glycol, 40%, alcohol, 10% and water for injection, to volume. The pH is adjusted to approximately 9.5 with hydrochloric acid and/or sodium hydroxide.

NEMBUTAL Sodium is a short-acting barbiturate, chemically designated as sodium 5-ethyl-5-(1-methylbutyl) barbiturate. The structural formula for pentobarbital sodium is:

The sodium salt occurs as a white, slightly bitter powder which is freely soluble in water and alcohol but practically insoluble in benzene and ether.

CLINICAL PHARMACOLOGY

Barbiturates are capable of producing all levels of CNS mood alteration from excitation to mild sedation, to hypnosis, and deep coma. Overdosage can produce death. In high enough therapeutic doses, barbiturates induce anesthesia.

Barbiturates depress the sensory cortex, decrease motor activity, alter cerebellar function, and produce drowsiness, sedation, and hypnosis.

Barbiturate-induced sleep differs from physiological sleep. Sleep laboratory studies have demonstrated that barbiturates reduce the amount of time spent in the rapid eye movement (REM) phase of sleep or dreaming stage. Also, Stages III and IV sleep are decreased. Following abrupt cessation of barbiturates used regularly, patients may experience markedly increased dreaming, nightmares, and/or insomnia. Therefore, withdrawal of a single therapeutic dose over 5 or 6 days has been recommended to lessen the REM rebound and disturbed sleep which contribute to drug withdrawal syndrome (for example, decrease the dose from 3 to 2 doses a day for 1 week).

In studies, secobarbital sodium and pentobarbital sodium have been found to lose most of their effectiveness for both inducing and maintaining sleep by the end of 2 weeks of continued drug administration at fixed doses. The short-, intermediate-, and, to a lesser degree, long-acting barbiturates have been widely prescribed for treating insomnia. Although the clinical literature abounds with claims that the short-acting barbiturates are superior for producing sleep while the intermediate-acting compounds are more effective in maintaining sleep, controlled studies have failed to demonstrate these differential effects. Therefore, as sleep medications, the barbiturates are of limited value beyond short-term use.

Barbiturates have little analgesic action at subanesthetic doses. Rather, in subanesthetic doses these drugs may increase the reaction to painful stimuli. All barbiturates exhibit anticonvulsant activity in anesthetic doses. However, of the drugs in this class, only phenobarbital, mephobarbital, and metharbital have been clinically demonstrated to be effective as oral anticonvulsants in subhypnotic doses.

Barbiturates are respiratory depressants. The degree of respiratory depression is dependent upon dose. With hypnotic doses, respiratory depression produced by barbiturates is similar to that which occurs during physiologic sleep with slight decrease in blood pressure and heart rate.

Studies in laboratory animals have shown that barbiturates cause reduction in the tone and contractility of the uterus, ureters, and urinary bladder. However, concentrations of the drugs required to produce this effect in humans are not reached with sedative-hypnotic doses.

Barbiturates do not impair normal hepatic function, but have been shown to induce liver microsomal enzymes, thus increasing and/or altering the metabolism of barbiturates and other drugs. (See “Precautions-Drug Interactions” section).

Pharmacokinetics:

Barbiturates are absorbed in varying degrees following oral, rectal, or parenteral administration. The salts are more rapidly absorbed than are the acids.

The onset of action for oral or rectal administration varies from 20 to 60 minutes. For IM administration, the onset of action is slightly faster. Following IV administration, the onset of action ranges from almost immediately for pentobarbital sodium to 5 minutes for phenobarbital sodium. Maximal CNS depression may not occur until 15 minutes or more after IV administration for phenobarbital sodium.

Duration of action, which is related to the rate at which the barbiturates are redistributed throughout the body, varies among persons and in the same person from time to time.

No studies have demonstrated that the different routes of administration are equivalent with respect to bioavailability.

Barbiturates are weak acids that are absorbed and rapidly distributed to all tissues and fluids with high concentrations in the brain, liver, and kidneys. Lipid solubility of the barbiturates is the dominant factor in their distribution within the body. The more lipid soluble the barbiturate, the more rapidly it penetrates all tissues of the body. Barbiturates are bound to plasma and tissue proteins to a varying degree with the degree of binding increasing directly as a function of lipid solubility.

Phenobarbital has the lowest lipid solubility, lowest plasma binding, lowest brain protein binding, the longest delay in onset of activity, and the longest duration of action. At the opposite extreme is secobarbital which has the highest lipid solubility, plasma protein binding, brain protein binding, the shortest delay in onset of activity, and the shortest duration of action. Butabarbital is classified as an intermediate barbiturate.

The plasma half-life for pentobarbital in adults is 15 to 50 hours and appears to be dose dependent.

Barbiturates are metabolized primarily by the hepatic microsomal enzyme system, and the metabolic products are excreted in the urine, and less commonly, in the feces. Approximately 25 to 50 percent of a dose of aprobarbital or phenobarbital is eliminated unchanged in the urine, whereas the amount of other barbiturates excreted unchanged in the urine is negligible. The excretion of unmetabolized barbiturate is one feature that distinguishes the long-acting category from those belonging to other categories which are almost entirely metabolized. The inactive metabolites of the barbiturates are excreted as conjugates of glucuronic acid.

INDICATIONS AND USAGE

Parenteral:

1. Sedatives.
2. Hypnotics, for the short-term treatment of insomnia, since they appear to lose their effectiveness for sleep induction and sleep maintenance after 2 weeks (See “Clinical Pharmacology” section.)
3. Preanesthetics.
4. Anticonvulsant, in anesthetic doses, in the emergency control of certain acute convulsive episodes, e.g., those associated with status epilepticus, cholera, eclampsia, meningitis, tetanus, and toxic reactions to strychnine or local anesthetics.

CONTRAINDICATIONS

Barbiturates are contraindicated in patients with known barbiturate sensitivity. Barbiturates are also contraindicated in patients with a history of manifest or latent porphyria.

WARNINGS

1. Habit forming : Barbiturates may be habit forming. Tolerance, psychological and physical dependence may occur with continued use. (See “Drug Abuse and Dependence” and “Pharmacokinetics” sections.) Patients who have psychological dependence on barbiturates may increase the dosage or decrease the dosage interval without consulting a physician and may subsequently develop a physical dependence on barbiturates. To minimize the possibility of overdosage or the development of dependence, the prescribing and dispensing of sedative-hypnotic barbiturates should be limited to the amount required for the interval until the next appointment. Abrupt cessation after prolonged use in the dependent person may result in withdrawal symptoms, including delirium, convulsions, and possibly death. Barbiturates should be withdrawn gradually from any patient known to be taking excessive dosage over long periods of time. (See “Drug Abuse and Dependence” section.)
2. IV administration: Too rapid administration may cause respiratory depression, apnea, laryngospasm, or vasodilation with fall in blood pressure.
3. Acute or chronic pain: Caution should be exercised when barbiturates are administered to patients with acute or chronic pain, because paradoxical excitement could be induced or important symptoms could be masked. However, the use of barbiturates as sedatives in the postoperative surgical period and as adjuncts to cancer chemotherapy is well established.
4. Use in pregnancy: Barbiturates can cause fetal damage when administered to a pregnant woman. Retrospective, case-controlled studies have suggested a connection between the maternal consumption of barbiturates and a higher than expected incidence of fetal abnormalities. Following oral or parenteral administration, barbiturates readily cross the placental barrier and are distributed throughout fetal tissues with highest concentrations found in the placenta, fetal liver, and brain. Fetal blood levels approach maternal blood levels following parenteral administration.
  Withdrawal symptoms occur in infants born to mothers who receive barbiturates throughout the last trimester of pregnancy. (See “Drug Abuse and Dependence” section.) If this drug is used during pregnancy, or if the patient becomes pregnant while taking this drug, the patient should be apprised of the potential hazard to the fetus.
5. Synergistic effects: The concomitant use of alcohol or other CNS depressants may produce additive CNS depressant effects.
6. Pediatric neurotoxicity: Published animal studies demonstrate that the administration of anesthetic and sedation drugs that block NMDA receptors and/or potentiate GABA activity increase neuronal apoptosis in the developing brain and result in long-term cognitive deficits when used for longer than 3 hours. The clinical significance of these findings is not clear. However, based on the available data, the window of vulnerability to these changes is believed to correlate with exposures in the third trimester of gestation through the first several months of life, but may extend out to approximately three years of age in humans (see “Precautions-Pregnancy and Pediatric Use” and “Animal Pharmacology and/or Toxicology”).
  Some published studies in children suggest that similar deficits may occur after repeated or prolonged exposures to anesthetic agents early in life and may result in adverse cognitive or behavioral effects. These studies have substantial limitations, and it is not clear if the observed effects are due to the anesthetic/sedation drug administration or other factors such as the surgery or underlying illness.
  Anesthetic and sedation drugs are a necessary part of the care of children and pregnant women needing surgery, other procedures, or tests that cannot be delayed, and no specific medications have been shown to be safer than any other. Decisions regarding the timing of any elective procedures requiring anesthesia should take into consideration the benefits of the procedure weighed against the potential risks.

PRECAUTIONS

General:

Barbiturates may be habit forming. Tolerance and psychological and physical dependence may occur with continuing use. (See “Drug Abuse and Dependence” section.) Barbiturates should be administered with caution, if at all, to patients who are mentally depressed, have suicidal tendencies, or a history of drug abuse.

Elderly or debilitated patients may react to barbiturates with marked excitement, depression, and confusion. In some persons, barbiturates repeatedly produce excitement rather than depression.

In patients with hepatic damage, barbiturates should be administered with caution and initially in reduced doses. Barbiturates should not be administered to patients showing the premonitory signs of hepatic coma.

Parenteral solutions of barbiturates are highly alkaline. Therefore, extreme care should be taken to avoid perivascular extravasation or intra-arterial injection. Extravascular injection may cause local tissue damage with subsequent necrosis; consequences of intra-arterial injection may vary from transient pain to gangrene of the limb. Any complaint of pain in the limb warrants stopping the injection.

Information for the patient:

Practitioners should give the following information and instructions to patients receiving barbiturates.

1. The use of barbiturates carries with it an associated risk of psychological and/or physical dependence. The patient should be warned against increasing the dose of the drug without consulting a physician.
2. Barbiturates may impair mental and/or physical abilities required for the performance of potentially hazardous tasks (e.g., driving, operating machinery, etc.).
3. Alcohol should not be consumed while taking barbiturates. Concurrent use of the barbiturates with other CNS depressants (e.g., alcohol, narcotics, tranquilizers, and antihistamines) may result in additional CNS depressant effects.
4. Effect of anesthetic and sedation drugs on early brain development
  Studies conducted in young animals and children suggest repeated or prolonged use of general anesthetic or sedation drugs in children younger than 3 years may have negative effects on their developing brains. Discuss with parents and caregivers the benefits, risks, and timing and duration of surgery or procedures requiring anesthetic and sedation drugs. Because some animal data suggest that the window of vulnerability includes the 3rd trimester of pregnancy, discuss with pregnant women the benefits, risks, and timing and duration of surgery or procedures requiring anesthetic and sedation drugs. (See “Warnings-Pediatric Neurotoxicity”.)

Laboratory tests:

Prolonged therapy with barbiturates should be accompanied by periodic laboratory evaluation of organ systems, including hematopoietic, renal, and hepatic systems. (See “Precautions-General” and “Adverse Reactions” sections.)

Drug interactions:

Most reports of clinically significant drug interactions occurring with the barbiturates have involved phenobarbital. However, the application of these data to other barbiturates appears valid and warrants serial blood level determinations of the relevant drugs when there are multiple therapies.

1. Anticoagulants: Phenobarbital lowers the plasma levels of dicumarol (name previously used: bishydroxycoumarin) and causes a decrease in anticoagulant activity as measured by the prothrombin time. Barbiturates can induce hepatic microsomal enzymes resulting in increased metabolism and decreased anticoagulant response of oral anticoagulants (e.g., warfarin, acenocoumarol, dicumarol, and phenprocoumon). Patients stabilized on anticoagulant therapy may require dosage adjustments if barbiturates are added to or withdrawn from their dosage regimen.
2. Corticosteroids: Barbiturates appear to enhance the metabolism of exogenous corticosteroids probably through the induction of hepatic microsomal enzymes. Patients stabilized on corticosteroid therapy may require dosage adjustments if barbiturates are added to or withdrawn from their dosage regimen.
3. Griseofulvin: Phenobarbital appears to interfere with the absorption of orally administered griseofulvin, thus decreasing its blood level. The effect of the resultant decreased blood levels of griseofulvin on therapeutic response has not been established. However, it would be preferable to avoid concomitant administration of these drugs.
4. Doxycycline: Phenobarbital has been shown to shorten the half-life of doxycycline for as long as 2 weeks after barbiturate therapy is discontinued.
  This mechanism is probably through the induction of hepatic microsomal enzymes that metabolize the antibiotic. If phenobarbital and doxycycline are administered concurrently, the clinical response to doxycycline should be monitored closely.
5. Phenytoin, sodium valproate, valproic acid: The effect of barbiturates on the metabolism of phenytoin appears to be variable. Some investigators report an accelerating effect, while others report no effect. Because the effect of barbiturates on the metabolism of phenytoin is not predictable, phenytoin and barbiturate blood levels should be monitored more frequently if these drugs are given concurrently. Sodium valproate and valproic acid appear to decrease barbiturate metabolism; therefore, barbiturate blood levels should be monitored and appropriate dosage adjustments made as indicated.
6. Central nervous system depressants: The concomitant use of other central nervous system depressants, including other sedatives or hypnotics, antihistamines, tranquilizers, or alcohol, may produce additive depressant effects.
7. Monoamine oxidase inhibitors (MAOI): MAOI prolong the effects of barbiturates probably because metabolism of the barbiturate is inhibited.
8. Estradiol, estrone, progesterone and other steroidal hormones: Pretreatment with or concurrent administration of phenobarbital may decrease the effect of estradiol by increasing its metabolism. There have been reports of patients treated with antiepileptic drugs (e.g., phenobarbital) who became pregnant while taking oral contraceptives. An alternate contraceptive method might be suggested to women taking phenobarbital.

Carcinogenesis:

1. Animal data. Phenobarbital sodium is carcinogenic in mice and rats after lifetime administration. In mice, it produced benign and malignant liver cell tumors. In rats, benign liver cell tumors were observed very late in life.
2. Human data. In a 29-year epidemiological study of 9,136 patients who were treated on an anticonvulsant protocol that included phenobarbital, results indicated a higher than normal incidence of hepatic carcinoma. Previously, some of these patients were treated with thorotrast, a drug that is known to produce hepatic carcinomas. Thus, this study did not provide sufficient evidence that phenobarbital sodium is carcinogenic in humans.

Data from one retrospective study of 235 children in which the types of barbiturates are not identified suggested an association between exposure to barbiturates prenatally and an increased incidence of brain tumor. (Gold, E., et al., “Increased Risk of Brain Tumors in Children Exposed to Barbiturates,” Journal of National Cancer Institute, 61:1031-1034, 1978).

Pregnancy:

1. Teratogenic effects. Pregnancy Category D—See “Warnings-Use in Pregnancy” section.
2. Nonteratogenic effects. Reports of infants suffering from long-term barbiturate exposure in utero included the acute withdrawal syndrome of seizures and hyperirritability from birth to a delayed onset of up to 14 days. (See “Drug Abuse and Dependence” section.)
3. Published studies in pregnant primates demonstrate that the administration of anesthetic and sedation drugs that block NMDA receptors and/or potentiate GABA activity during the period of peak brain development increases neuronal apoptosis in the developing brain of the offspring when used for longer than 3 hours. There are no data on pregnancy exposures in primates corresponding to periods prior to the third trimester in humans.
  In a published study, administration of an anesthetic dose of ketamine for 24 hours on Gestation Day 122 increased neuronal apoptosis in the developing brain of the fetus. In other published studies, administration of either isoflurane or propofol for 5 hours on Gestation Day 120 resulted in increased neuronal and oligodendrocyte apoptosis in the developing brain of the offspring. With respect to brain development, this time period corresponds to the third trimester of gestation in the human. The clinical significance of these findings is not clear; however, studies in juvenile animals suggest neuroapoptosis correlates with long-term cognitive deficits (see “Warnings-Pediatric Neurotoxicity”, “Precautions Pediatric Use”, and “Animal Pharmacology and/or Toxicology”).

Labor and delivery:

Hypnotic doses of these barbiturates do not appear to significantly impair uterine activity during labor. Full anesthetic doses of barbiturates decrease the force and frequency of uterine contractions. Administration of sedative-hypnotic barbiturates to the mother during labor may result in respiratory depression in the newborn. Premature infants are particularly susceptible to the depressant effects of barbiturates. If barbiturates are used during labor and delivery, resuscitation equipment should be available.

Data are currently not available to evaluate the effect of these barbiturates when forceps delivery or other intervention is necessary. Also, data are not available to determine the effect of these barbiturates on the later growth, development, and functional maturation of the child.

Nursing mothers:

Caution should be exercised when a barbiturate is administered to a nursing woman since small amounts of barbiturates are excreted in the milk.

Pediatric use:

No adequate well-controlled studies have been conducted in pediatric patients; however, safety and effectiveness of pentobarbital in pediatric patients is supported by numerous studies and case reports cited in the literature.

Pediatric dosing information for Nembutal is described in the DOSAGE AND ADMINISTRATION section.

Published juvenile animal studies demonstrate that the administration of anesthetic and sedation drugs, such as Pentobarbital Sodium Injection USP, (Nembutal) that either block NMDA receptors or potentiate the activity of GABA during the period of rapid brain growth or synaptogenesis, results in widespread neuronal and oligodendrocyte cell loss in the developing brain and alterations in synaptic morphology and neurogenesis. Based on comparisons across species, the window of vulnerability to these changes is believed to correlate with exposures in the third trimester of gestation through the first several months of life, but may extend out to approximately 3 years of age in humans.

In primates, exposure to 3 hours of ketamine that produced a light surgical plane of anesthesia did not increase neuronal cell loss, however, treatment regimens of 5 hours or longer of isoflurane increased neuronal cell loss. Data from isoflurane-treated rodents and ketamine-treated primates suggest that the neuronal and oligodendrocyte cell losses are associated with prolonged cognitive deficits in learning and memory. The clinical significance of these nonclinical findings is not known, and healthcare providers should balance the benefits of appropriate anesthesia in pregnant women, neonates, and young children who require procedures with the potential risks suggested by the nonclinical data. (See “Warnings Pediatric Neurotoxicity”, “Precautions-Pregnancy”, and “Animal Pharmacology and/or Toxicology”.)

Geriatric use:

Clinical studies of Nembutal have not included sufficient numbers of subjects aged 65 and over to determine whether elderly subjects respond differently from younger subjects. Other reported clinical experience has not identified differences in responses between the elderly and younger patients. In general, dose selection for an elderly patient should be cautious, usually starting at the low end of the dosing range, reflecting the greater frequency of decreased hepatic, renal or cardiac function, and of concomitant disease or other drug therapy.

Elderly patients may react to barbiturates with marked excitement, depression, and confusion. In some persons, barbiturates repeatedly produce excitement rather than depression. Dosage should be reduced in the elderly because these patients may be more sensitive to barbiturates.

ADVERSE REACTIONS

The following adverse reactions and their incidence were compiled from surveillance of thousands of hospitalized patients. Because such patients may be less aware of certain of the milder adverse effects of barbiturates, the incidence of these reactions may be somewhat higher in fully ambulatory patients.

More than 1 in 100 patients. The most common adverse reaction estimated to occur at a rate of 1 to 3 patients per 100 is: Nervous System: Somnolence.

Less than 1 in 100 patients. Adverse reactions estimated to occur at a rate of less than 1 in 100 patients listed below, grouped by organ system, and by decreasing order of occurrence are:

Nervous system: Agitation, confusion, hyperkinesia, ataxia, CNS depression, nightmares, nervousness, psychiatric disturbance, hallucinations, insomnia, anxiety, dizziness, thinking abnormality.

Respiratory system: Hypoventilation, apnea.

Cardiovascular system: Bradycardia, hypotension, syncope.

Digestive system: Nausea, vomiting, constipation.

Other reported reactions: Headache, injection site reactions, hypersensitivity reactions (angioedema, skin rashes, exfoliative dermatitis), fever, liver damage, megaloblastic anemia following chronic phenobarbital use.

To report SUSPECTED ADVERSE REACTIONS, contact Oak Pharmaceuticals, Inc. at 1-800-932-5676 or FDA at 1-800-FDA-1088 or www.fda.gov/medwatch.

DRUG ABUSE AND DEPENDENCE

Pentobarbital sodium injection is subject to control by the Federal Controlled Substances Act under DEA schedule II.

Barbiturates may be habit forming. Tolerance, psychological dependence, and physical dependence may occur especially following prolonged use of high doses of barbiturates. Daily administration in excess of 400 milligrams (mg) of pentobarbital or secobarbital for approximately 90 days is likely to produce some degree of physical dependence. A dosage of from 600 to 800 mg taken for at least 35 days is sufficient to produce withdrawal seizures. The average daily dose for the barbiturate addict is usually about 1.5 grams. As tolerance to barbiturates develops, the amount needed to maintain the same level of intoxication increases; tolerance to a fatal dosage, however, does not increase more than two-fold. As this occurs, the margin between an intoxicating dosage and fatal dosage becomes smaller.

Symptoms of acute intoxication with barbiturates include unsteady gait, slurred speech, and sustained nystagmus. Mental signs of chronic intoxication include confusion, poor judgment, irritability, insomnia, and somatic complaints.

Symptoms of barbiturate dependence are similar to those of chronic alcoholism. If an individual appears to be intoxicated with alcohol to a degree that is radically disproportionate to the amount of alcohol in his or her blood the use of barbiturates should be suspected. The lethal dose of a barbiturate is far less if alcohol is also ingested.

The symptoms of barbiturate withdrawal can be severe and may cause death. Minor withdrawal symptoms may appear 8 to 12 hours after the last dose of a barbiturate. These symptoms usually appear in the following order: anxiety, muscle twitching, tremor of hands and fingers, progressive weakness, dizziness, distortion in visual perception, nausea, vomiting, insomnia, and orthostatic hypotension. Major withdrawal symptoms (convulsions and delirium) may occur within 16 hours and last up to 5 days after abrupt cessation of these drugs. Intensity of withdrawal symptoms gradually declines over a period of approximately 15 days. Individuals susceptible to barbiturate abuse and dependence include alcoholics and opiate abusers, as well as other sedative-hypnotic and amphetamine abusers.

Drug dependence to barbiturates arises from repeated administration of a barbiturate or agent with barbiturate-like effect on a continuous basis, generally in amounts exceeding therapeutic dose levels. The characteristics of drug dependence to barbiturates include: (a) a strong desire or need to continue taking the drug; (b) a tendency to increase the dose; (c) a psychic dependence on the effects of the drug related to subjective and individual appreciation of those effects; and (d) a physical dependence on the effects of the drug requiring its presence for maintenance of homeostasis and resulting in a definite, characteristic, and self-limited abstinence syndrome when the drug is withdrawn.

Treatment of barbiturate dependence consists of cautious and gradual withdrawal of the drug. Barbiturate-dependent patients can be withdrawn by using a number of different withdrawal regimens. In all cases withdrawal takes an extended period of time. One method involves substituting a 30 mg dose of phenobarbital for each 100 to 200 mg dose of barbiturate that the patient has been taking. The total daily amount of phenobarbital is then administered in 3 to 4 divided doses, not to exceed 600 mg daily. Should signs of withdrawal occur on the first day of treatment, a loading dose of 100 to 200 mg of phenobarbital may be administered IM in addition to the oral dose. After stabilization on phenobarbital, the total daily dose is decreased by 30 mg a day as long as withdrawal is proceeding smoothly. A modification of this regimen involves initiating treatment at the patient's regular dosage level and decreasing the daily dosage by 10 percent if tolerated by the patient.

Infants physically dependent on barbiturates may be given phenobarbital 3 to 10 mg/kg/day. After withdrawal symptoms (hyperactivity, disturbed sleep, tremors, hyperreflexia) are relieved, the dosage of phenobarbital should be gradually decreased and completely withdrawn over a 2-week period.

OVERDOSAGE

The toxic dose of barbiturates varies considerably. In general, an oral dose of 1 gram of most barbiturates produces serious poisoning in an adult. Death commonly occurs after 2 to 10 grams of ingested barbiturate. Barbiturate intoxication may be confused with alcoholism, bromide intoxication, and with various neurological disorders.

Acute overdosage with barbiturates is manifested by CNS and respiratory depression which may progress to Cheyne-Stokes respiration, areflexia, constriction of the pupils to a slight degree (though in severe poisoning they may show paralytic dilation), oliguria, tachycardia, hypotension, lowered body temperature, and coma. Typical shock syndrome (apnea, circulatory collapse, respiratory arrest, and death) may occur.

In extreme overdose, all electrical activity in the brain may cease, in which case a “flat” EEG normally equated with clinical death cannot be accepted. This effect is fully reversible unless hypoxic damage occurs. Consideration should be given to the possibility of barbiturate intoxication even in situations that appear to involve trauma.

Complications such as pneumonia, pulmonary edema, cardiac arrhythmias, congestive heart failure, and renal failure may occur. Uremia may increase CNS sensitivity to barbiturates. Differential diagnosis should include hypoglycemia, head trauma, cerebrovascular accidents, convulsive states, and diabetic coma. Blood levels from acute overdosage for some barbiturates are listed in Table 1.

Table 1. Concentration of Barbiturate in the Blood Versus Degree of CNS Depression
Blood barbiturate level in ppm (μg/mL)
Barbiturate | Onset/duration | Degree of depression in nontolerant persons*
Barbiturate | Onset/duration | 1 | 2 | 3 | 4 | 5
Pentobarbital | Fast/short | ≤2 | 0.5 to 3 | 10 to 15 | 12 to 25 | 15 to 40
Secobarbital | Fast/short | ≤2 | 0.5 to 5 | 10 to 15 | 15 to 25 | 15 to 40
Amobarbital | Intermediate/ intermediate | ≤3 | 2 to 10 | 30 to 40 | 30 to 60 | 40 to 80
Butabarbital | Intermediate/ intermediate | ≤5 | 3 to 25 | 40 to 60 | 50 to 80 | 60 to 100
Phenobarbital | Slow/long | ≤10 | 5 to 40 | 50 to 80 | 70 to 120 | 100 to 200
*Categories of degree of depression in nontolerant persons:

1. Under the influence and appreciably impaired for purposes of driving a motor vehicle or performing tasks requiring alertness and unimpaired judgment and reaction time.
2. Sedated, therapeutic range, calm, relaxed, and easily aroused.
3. Comatose, difficult to arouse, significant depression of respiration.
4. Compatible with death in aged or ill persons or in presence of obstructed airway, other toxic agents, or exposure to cold.
5. Usual lethal level, the upper end of the range includes those who received some supportive treatment.

Treatment of overdosage is mainly supportive and consists of the following:

1. Maintenance of an adequate airway, with assisted respiration and oxygen administration as necessary.
2. Monitoring of vital signs and fluid balance.
3. Fluid therapy and other standard treatment for shock, if needed.
4. If renal function is normal, forced diuresis may aid in the elimination of the barbiturate. Alkalinization of the urine increases renal excretion of some barbiturates, especially phenobarbital, also aprobarbital and mephobarbital (which is metabolized to phenobarbital).
5. Although not recommended as a routine procedure, hemodialysis may be used in severe barbiturate intoxications or if the patient is anuric or in shock.
6. Patient should be rolled from side to side every 30 minutes.
7. Antibiotics should be given if pneumonia is suspected.
8. Appropriate nursing care to prevent hypostatic pneumonia, decubiti, aspiration, and other complications of patients with altered states of consciousness.

DOSAGE AND ADMINISTRATION

Dosages of barbiturates must be individualized with full knowledge of their particular characteristics and recommended rate of administration. Factors of consideration are the patient's age, weight, and condition. Parenteral routes should be used only when oral administration is impossible or impractical.

Intramuscular Administration: IM injection of the sodium salts of barbiturates should be made deeply into a large muscle, and a volume of 5 mL should not be exceeded at any one site because of possible tissue irritation. After IM injection of a hypnotic dose, the patient's vital signs should be monitored. The usual adult dosage of NEMBUTAL Sodium Solution is 150 to 200 mg as a single IM injection; the recommended pediatric dosage ranges from 2 to 6 mg/kg as a single IM injection not to exceed 100 mg.

Intravenous Administration: NEMBUTAL Sodium Solution should not be admixed with any other medication or solution. IV injection is restricted to conditions in which other routes are not feasible, either because the patient is unconscious (as in cerebral hemorrhage, eclampsia, or status epilepticus), or because the patient resists (as in delirium), or because prompt action is imperative. Slow IV injection is essential, and patients should be carefully observed during administration. This requires that blood pressure, respiration, and cardiac function be maintained, vital signs be recorded, and equipment for resuscitation and artificial ventilation be available. The rate of IV injection should not exceed 50 mg/min for pentobarbital sodium.

There is no average intravenous dose of NEMBUTAL Sodium Solution (pentobarbital sodium injection) that can be relied on to produce similar effects in different patients. The possibility of overdose and respiratory depression is remote when the drug is injected slowly in fractional doses.

A commonly used initial dose for the 70 kg adult is 100 mg. Proportional reduction in dosage should be made for pediatric or debilitated patients. At least one minute is necessary to determine the full effect of intravenous pentobarbital. If necessary, additional small increments of the drug may be given up to a total of from 200 to 500 mg for normal adults.

Anticonvulsant use: In convulsive states, dosage of NEMBUTAL Sodium Solution should be kept to a minimum to avoid compounding the depression which may follow convulsions. The injection must be made slowly with due regard to the time required for the drug to penetrate the blood-brain barrier.

Special patient population: Dosage should be reduced in the elderly or debilitated because these patients may be more sensitive to barbiturates. Dosage should be reduced for patients with impaired renal function or hepatic disease.

Inspection: Parenteral drug products should be inspected visually for particulate matter and discoloration prior to administration, whenever solution containers permit. Solutions for injection showing evidence of precipitation should not be used.

HOW SUPPLIED

NEMBUTAL Sodium Solution (pentobarbital sodium injection, USP) is available in the following sizes: 20-mL multiple-dose vial, 1 g per vial (NDC 17478-181-20); and 50-mL multiple-dose vial, 2.5 g per vial (NDC 17478-181-50).

Each mL contains:

Pentobarbital Sodium, derivative of barbituric acid………………………………………… 50 mg

Propylene glycol……………………………………………………………………………40% v/v

Alcohol…………………………………………………………………………………… 10%

Water for Injection………………………………………………………………………… qs

(pH adjusted to approximately 9.5 with hydrochloric acid and/or sodium hydroxide.)

Vial stoppers are latex free.

Exposure of pharmaceutical products to heat should be minimized. Avoid excessive heat. Protect from freezing. It is recommended that the product be stored at 20° to 25°C (68° to 77°F), however, brief excursions are permitted between 15° to 30°C (59° to 86°F). See USP controlled room temperature.

ANIMAL PHARMACOLOGY AND/OR TOXICOLOGY

Published studies in animals demonstrate that the use of anesthetic agents during the period of rapid brain growth or synaptogenesis results in widespread neuronal and oligodendrocyte cell loss in the developing brain and alterations in synaptic morphology and neurogenesis. Based on comparisons across species, the window of vulnerability to these changes is believed to correlate with exposures in the third trimester through the first several months of life, but may extend out to approximately 3 years of age in humans.

In primates, exposure to 3 hours of exposure to an anesthetic regimen that produced a light surgical plane of anesthesia did not increase neuronal cell loss, however, treatment regimens of 5 hours or longer increased neuronal cell loss. Data in rodents and in primates suggest that the neuronal and oligodendrocyte cell losses are associated with subtle but prolonged cognitive deficits in learning and memory. The clinical significance of these nonclinical findings is not known, and healthcare providers should balance the benefits of appropriate anesthesia in neonates and young children who require procedures against the potential risks suggested by the nonclinical data (see “Warnings-Pediatric Neurotoxicity” and “Precautions-Pregnancy and Pediatric Use”).

novaplus TM^+

Manufactured by: Akorn, Inc.
Lake Forest, IL 60045

® Trademark of Oak Pharmaceuticals, Inc.

Novaplus is a registered trademark of Vizient, Inc.

NPNM00N Rev. 02/20

Principal Display Panel Text for Container Label:

NDC 17478-181-20 Rx ONLY

Nembutal® CII

Sodium Solution

(pentobarbital sodium injection, USP)

For Intravenous or

Intramuscular Use

50 mg/

mL

20 mL Sterile Solution

Multiple-dose Vial

novaplus™^+ LATEX-FREE

Principal Display Panel Text for Carton Label:

NDC 17478-181-20

Nembutal® CII

Sodium Solution

(pentobarbital sodium

injection, USP)

50 mg/

mL

For Intravenous

or Intramuscular Use

20 mL Sterile Solution

Multiple-dose Vial

LATEX-FREE

Caution: This solution is not suitable

for subcutaneous administration.

Rx ONLY

novaplus™^+